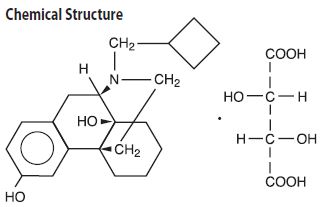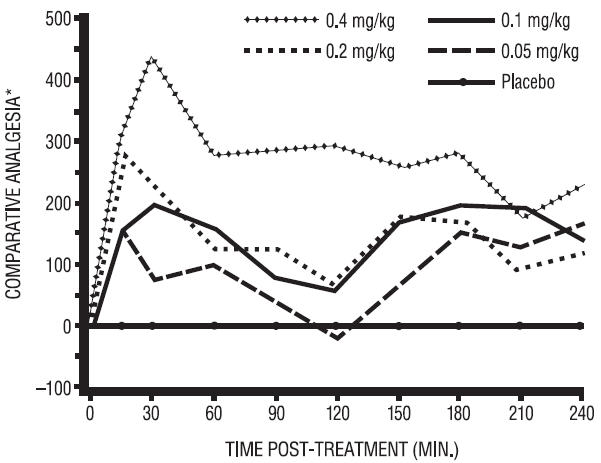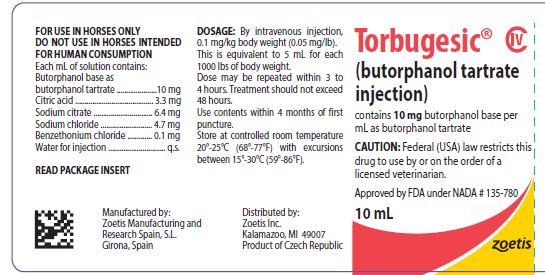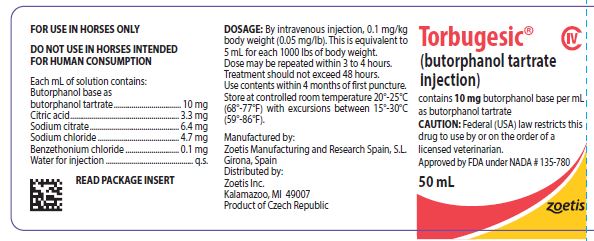 DRUG LABEL: Torbugesic
NDC: 54771-2033 | Form: SOLUTION
Manufacturer: Zoetis Inc.
Category: animal | Type: PRESCRIPTION ANIMAL DRUG LABEL
Date: 20200320
DEA Schedule: CIV

ACTIVE INGREDIENTS: BUTORPHANOL TARTRATE 10 mg/1 mL
INACTIVE INGREDIENTS: CITRIC ACID MONOHYDRATE 3.3 mg/1 mL; SODIUM CITRATE; SODIUM CHLORIDE; BENZETHONIUM CHLORIDE

Torbugesic®
(butorphanol tartrate injection)

Torbugesic®

(butorphanol tartrate injection)

CAUTION

Federal (USA) law restricts this drug to use by or on the order of a licensed veterinarian.

DESCRIPTION

TORBUGESIC (butorphanol tartrate injection) is a totally synthetic, centrally acting, narcotic agonist-antagonist analgesic with potent antitussive activity. It is a member of the phenanthrene series. The chemical name is Morphinan-3, 14-diol, 17-(cyclobutylmethyl)-, (-)-, (S- (R*, R*))-2,3-dihydroxybutanedioate (1:1) (salt). It is a white, crystalline, water soluble substance having a molecular weight of 477.55; its molecular formula is C21H29NO2•C4H6O6.

Chemical Structure

Each mL of TORBUGESIC contains 10 mg butorphanol base (as butorphanol tartrate), 3.3 mg citric acid, USP, 6.4 mg sodium citrate, 4.7 mg sodium chloride, and 0.1 mg benzethonium chloride, q.s. with water for injection.

CLINICAL PHARMACOLOGY

Comparative Pharmacology

In animals, butorphanol has been demonstrated to be 4 to 30 times more potent than morphine and pentazocine (Talwin®-V) respectively.^1

In humans, butorphanol has been shown to have 5 to 7 times the analgesic activity of morphine and 20 times that of pentazocine.^2,3

Butorphanol has 15 to 20 times the oral antitussive activity of codeine or dextromethorphan in dogs and guinea pigs.^4

As an antagonist, butorphanol is approximately equivalent to nalorphine and 30 times more potent than pentazocine.^1

Cardiopulmonary depressant effects are minimal after treatment with butorphanol as demonstrated in dogs^5, humans^6,7 and horses.^8

Unlike classical narcotic agonist analgesics which are associated with decreases in blood pressure, reduction in heart rate and concomitant release of histamine, butorphanol does not cause histamine release.^1

Furthermore, the cardiopulmonary effects of butorphanol are not distinctly dosage-related but rather reach a ceiling effect beyond which further
dosage increases result in relatively lesser effects.

Reproduction: Studies performed in mice and rabbits revealed no evidence of impaired fertility or harm to the fetus due to butorphanol tartrate. In the female rat, parenteral administration was associated with increased nervousness and decreased care for the newborn, resulting in a decreased survival rate of the newborn. This nervousness was seen only in the rat species.

Equine Pharmacology

Following intravenous injection in horses, butorphanol is largely eliminated from the blood within 3 to 4 hours. The drug is extensively metabolized in the liver and excreted in the urine. In ponies, butorphanol given intramuscularly at a dosage of 0.22 mg/kg, was shown to alleviate experimentally induced visceral pain for about 4 hours.^9

In horses, intravenous dosages of butorphanol ranging from 0.05 to 0.4 mg/kg were shown to be effective in alleviating visceral and superficial pain for at least 4 hours, as illustrated in the following figure:

Analgesic Effects of Butorphanol Given at
Various Dosages in Horses with Abdominal Pain

*Pain threshold in butorphanol-treated colicky horses relative to placebo controls.

A definite dosage-response relationship was detected in that butorphanol dosage of 0.1 mg/kg was more effective than 0.05 mg/kg but not different from 0.2 mg/kg in alleviating deep abdominal pain.

Acute Equine Studies

Rapid intravenous administration of butorphanol at a dosage of 2 mg/kg (20 times the recommended dosage) to a previously unmedicated horse resulted in a brief episode of inability to stand, muscle fasciculation, a convulsive seizure of 6 seconds duration and recovery within three minutes. The same dosage administered after 10 successive daily 1 mg/kg dosages of butorphanol resulted only in transient sedative effects. During the 10-day course of administration at 1 mg/kg (10 times the recommended use level) in two horses, the only detectable drug effects were transient behavioral changes typical of narcotic agonist activity. These included muscle fasciculation about the head and neck, dysphoria, lateral nystagmus, ataxia and salivation.

Repeated administration of butorphanol at 1 mg/kg (10 times the recommended dose) every four hours for 48 hours caused constipation in one of two horses.

Subacute Equine Studies

Horses were found to tolerate butorphanol given intravenously at dosages of 0.1, 0.3 and 0.5 mg/kg every 4 hours for 48 hours followed by once daily injections for a total of 21 days. The only detectable drug effects were slight transient ataxia observed occasionally in the high dosage group. No clinical, laboratory, or gross or histopathologic evidence of any butorphanol-related toxicity was encountered in the horses.

INDICATIONS

TORBUGESIC (butorphanol tartrate injection) is indicated for the relief of pain associated with colic in adult horses and yearlings. Clinical studies in the horse have shown that TORBUGESIC alleviates abdominal pain associated with torsion, impaction, intussusception, spasmodic and tympanic colic and postpartum pain.

WARNINGS

DO NOT USE IN HORSES INTENDED FOR HUMAN CONSUMPTION. NOT FOR HUMAN USE.

CAUTION

TORBUGESIC, a potent analgesic, should be used with caution with other sedative or analgesic drugs as these are likely to produce additive effects. There are no well-controlled studies using butorphanol in breeding horses, weanlings and foals. Therefore, the drug should not be used in these groups.

ADVERSE REACTIONS

In clinical trials in horses, the most commonly observed side effect was slight ataxia which lasted 3 to 10 minutes.

Marked ataxia was reported in 1.5% of the 327 horses treated. Mild sedation was reported in 9% of the horses.

DOSAGE

The recommended dosage in the horse is 0.1 mg of butorphanol per kilogram of body weight (0.05 mg/lb) by intravenous injection. This is equivalent to 5 mL of TORBUGESIC for each 1000 lbs body weight.

The dose may be repeated within 3 to 4 hours but treatment should not exceed 48 hours.

Use contents within 4 months of first puncture. Pre-clinical model studies and clinical field trials in horses demonstrate that the analgesic effects of TORBUGESIC are seen within 15 minutes following injection and persist for about 4 hours.

HOW SUPPLIED

50 mL vials TORBUGESIC (butorphanol tartrate injection) Veterinary Injection, 10 mg base activity per mL.

10 mL vials TORBUGESIC (butorphanol tartrate injection) Veterinary Injection, 10 mg base activity per mL.

Store at controlled room temperature 20°-25°C (68°-77°F) with excursions between 15°-30°C (59°-86°F).

REFERENCES

1. Pircio, A.W. et al: “The Pharmacology of Butorphanol,” Arch. Int. Pharmacodyn. Ther. 220 (2): 231–257, 1976.

2. Dobkin, A.B. et al: “Butorphanol and Pentazocinein Patients with Severe Postoperative Pain,” Clin. Pharmacol. Ther. 18: 547–553, 1975.

3. Gilbert, M.S. et al: “Intramuscular Butorphanol and Meperidine in Postoperative Pain,” Clin. Pharmacol. Ther. 20: 359 –364, 1976.

4. Cavanagh, R.L. et al: “Antitussive Properties of Butorphanol,” Arch. Int. Pharmacodyn. Ther. 220 (2):258–268, 1976.

5. Schurig, J.E. et al: “Eff ect of Butorphanol and Morphine on Pulmonary Mechanics, Arterial Blood Pressure, and Venous Plasma Histamine in the Anesthetized Dog,” Arch. Int. Pharmacodyn. Ther. 233: 296–304, 1978.

6. Nagashmina, H. et al: “Respiratory and Circulatory Effects of Intravenous Butorphanol and Morphine,” Clin. Pharmacol. Ther. 19:735–745, 1976.

7. Popio, K.A. et al: “Hemodynamic and Respiratory Effects of Morphine and Butorphanol,” Clin. Pharmacol. Ther. 23: 281–287, 1978.
8. Robertson, J.T. and Muir, W.W.: “Cardiopulmonary Effects of Butorphanol Tartrate in Horses,” Am. J. Vet. Res. 42: 41–44, 1981.
9. Kalpravidh, M. et al: “Effects of Butorphanol, Flunixin, Levorphanol, Morphine, Pentazocine zine in Ponies,” Am. J. Vet. Res. 45:217–223, 1984.

Approved by FDA under NADA # 135-780
zoetis
Manufactured by:
Zoetis Manufacturing and Research Spain, S.L.
Girona, Spain
Distributed by:
Zoetis Inc.
Kalamazoo, MI 49007
Revised: May 2019